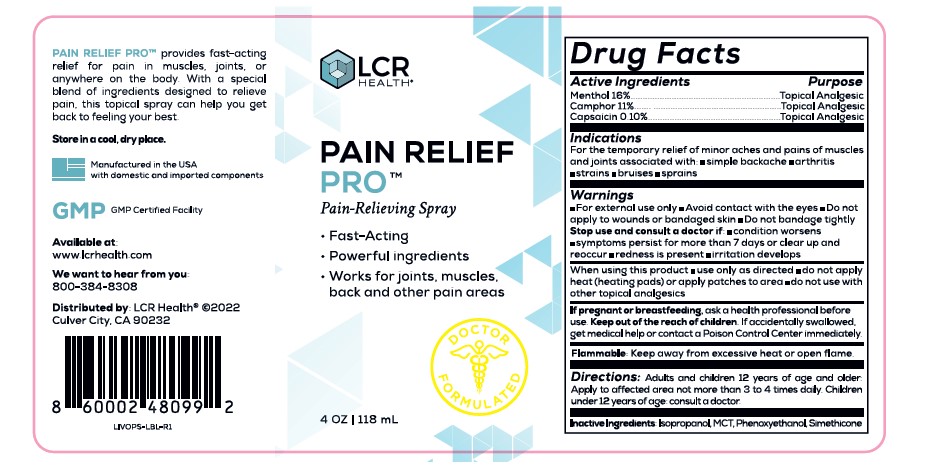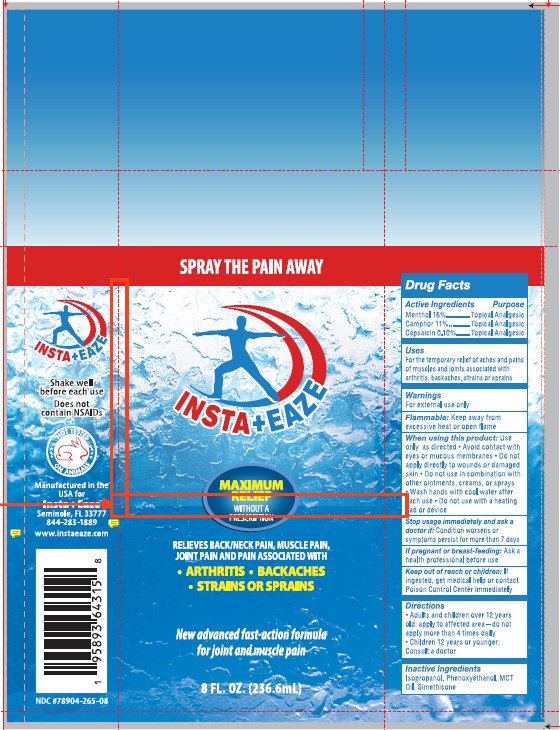 DRUG LABEL: Pain Away
NDC: 79804-265 | Form: SPRAY
Manufacturer: Eagle Labs Inc.
Category: otc | Type: HUMAN OTC DRUG LABEL
Date: 20240415

ACTIVE INGREDIENTS: MENTHOL 0.16 g/1 g; CAPSAICIN 0.001 g/1 g; CAMPHOR (SYNTHETIC) 0.11 g/1 g
INACTIVE INGREDIENTS: PALM OIL; ISOPROPYL ALCOHOL; SILICON DIOXIDE; PHENOXYETHANOL; DIMETHICONE

Pain Spray Extra Strength

ACTIVE INGREDIENT

Capsacin; Analgesic

Menthol: Analgesic

Camphor: Analgesic

PAIN RELIEF - TOPICAL ANALGESIC

Analgesic

Indications

For the temporary relief of minor aches and pains of muscles and joints associated with

Simple backache
Arthritis
Strains
Bruises
Sprains

Warnings

- For extrernal use only
- Avoid Contact with the eyes
- Do not apply to wounds or bandaged skin
- Do not bandage tightly

Stop use and consult a doctor if:

- Condition worsens
- Symptoms persist for more than 7 days or cleear up and reoccur
- Redness is present
- irritation develops

When using this product

- Use only as directed
- Do not apply heat (heating pads) or apply patches to area

Keep out of children

If accidentally swallowed get medical help or contact a poison control center immediately

If pregnant or breastfeeding, ask a health professional before use.

Keep out of the reach o children

If accidentally swallowed get medical help or contact a poison control center immediately

Flammable

Keep away from excessive heat or open flame

Flammable

Keep away from excessive heat or open flame

Inactive Ingredients

Isopropanol, MCT, Phenoxyethanol, Simethicone

Directions

Adults and children 12 years of age and older: Apply to affected area not more than 3 to 4 times daily. Children under 12 years of age consult a doctor.